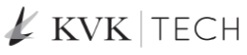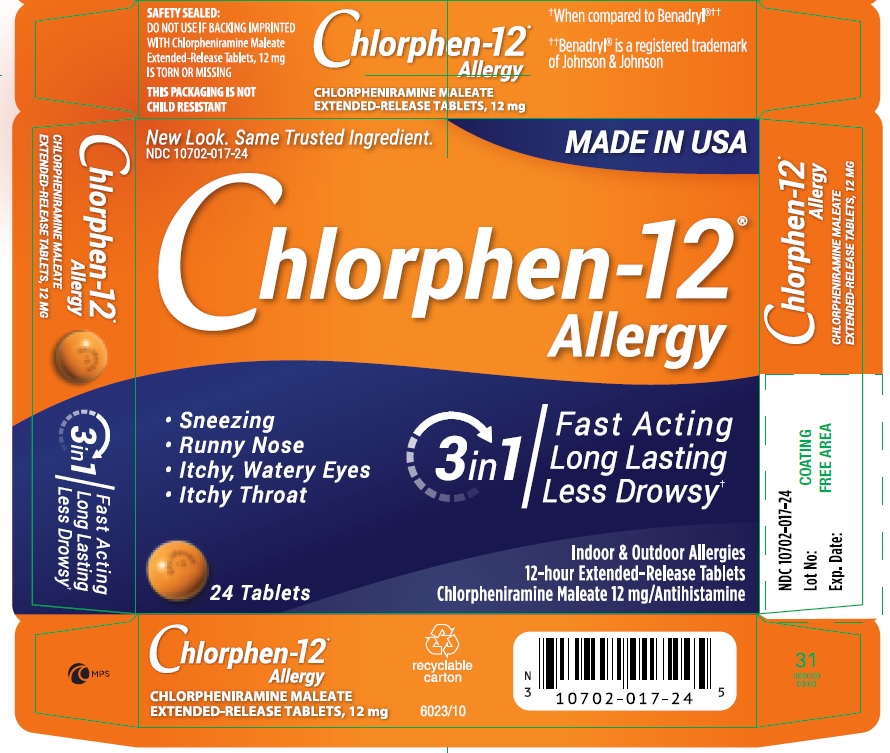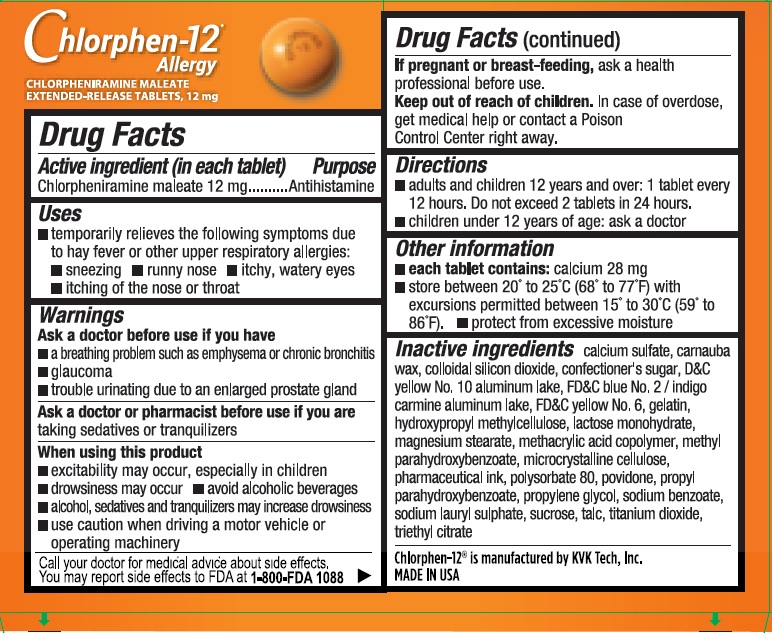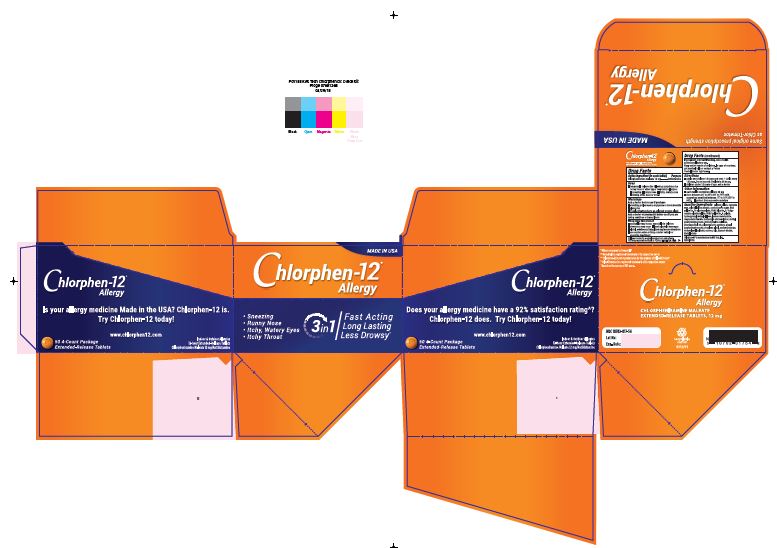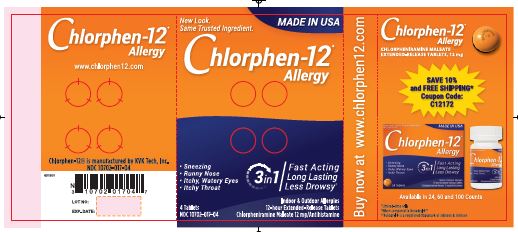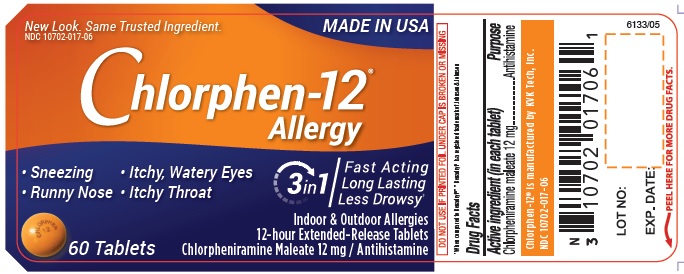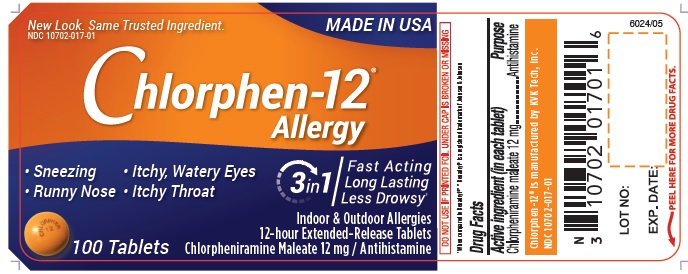 DRUG LABEL: Chlorphen-12
NDC: 10702-017 | Form: TABLET, FILM COATED, EXTENDED RELEASE
Manufacturer: KVK-Tech, Inc.
Category: otc | Type: HUMAN OTC DRUG LABEL
Date: 20181219

ACTIVE INGREDIENTS: CHLORPHENIRAMINE MALEATE 12 mg/1 1
INACTIVE INGREDIENTS: CALCIUM SULFATE; CARNAUBA WAX; SILICON DIOXIDE; SUCROSE; D&C YELLOW NO. 10; FD&C BLUE NO. 2; GELATIN; LOW-SUBSTITUTED HYDROXYPROPYL CELLULOSE, UNSPECIFIED; LACTOSE MONOHYDRATE; MAGNESIUM STEARATE; METHACRYLIC ACID - ETHYL ACRYLATE COPOLYMER (1:1) TYPE A; METHYLPARABEN; CELLULOSE, MICROCRYSTALLINE; POLYSORBATE 80; POVIDONE; PROPYLENE GLYCOL; SODIUM BENZOATE; SODIUM LAURETH SULFATE; TITANIUM DIOXIDE; TRIETHYL CITRATE; FD&C YELLOW NO. 6; TALC

Chlorphen-12 (Chlorpheniramine Maleate) Extended-Release Tablets, 12 mg

Chlorpheniramine maleate 12 mg

Antihistamine

USES

temporarily relieves the following symptoms due to hay fever or other upper respiratory allergies:
sneezing
runny nose
itchy, watery eyes
itching of the nose or throat

WARNINGS

Ask a doctor before use if you have
a breathing problem such as emphysema or chronic bronchitis
glaucoma
trouble urinating due to an enlarged prostate gland
Ask a doctor or pharmacist before use if you are
taking sedatives or tranquilizers
When using this product
excitability may occur, especially in children
drowsiness may occur
avoid alcoholic beverages
alchohol, sedatives and tranquilizers may increase drowsiness
use caution when driving a motor vehicle or operating machinery
Call your doctor for medical advice about side effects.
You may report side effects to FDA at 1-800-FDA-1088
If pregnant or breast-feeding, ask a health professional before use

KEEP OUT OF REACH OF CHILDREN

In case of overdose, get medical help or contact a Poison Control Center right away.

DIRECTIONS

- adults and children 12 years and over: 1 tablet every 12 hours. Do not exceed 2 tablets in 24 hours.
  children under 12 years of age: ask a doctor

OTHER INFORMATION

- each tablet contains: calcium 28 mg
  store between 20° to 25°C (68° to 77°F) with excursions permitted between 15° to 30°C (59° to 86°F)
  protect from excessive moisture

INACTIVE INGREDIENTS

- calcium sulfate, carnauba wax, colloidal silicon dioxide, confectioner’s sugar, D&C yellow No. 10 aluminum lake, FD&C blue No. 2/indigo carmine aluminum lake, FD&C yellow No. 6, gelatin, hydroxypropyl methylcellulose, lactose monohydrate, magnesium stearate, methacrylic acid copolymer, methyl parahydroxybenzoate, microcrystalline cellulose, pharmaceutical ink, polysorbate 80, povidone, propyl parahydroxybenzoate, propylene glycol, sodium benzoate, sodium lauryl sulphate, sucrose, talc, titanium dioxide, triethyl citrate

PURPOSE

Chlorpheniramine maleate 12 mg is used as an antihistamine.

Manufactured by:

KVK-Tech, Inc.
Newtown, PA 18940

Principal Display Panel - 24 Tablets Carton

New Look. Same Trusted Ingredient. MADE IN USA
NDC 10702-017-24

Chlorphen-12
Allergy

- Sneezing
- Runny Nose
- Itchy, Watery Eyes
- Itchy Throat

3 in 1
Fast Acting
Long Lasting
Less Drowsy

24 Tablets

Indoor & Outdoor Allergies
12-hour Extended-Release Tablets

Chlorpheniramine Maleate 12 mg/Antihistamine

Principal Display panel - 60 Tablets Container Label

New Look. Same Trusted Ingredient. MADE IN USA
NDC 10702-017-06

Chlorphen-12
Allergy

- Sneezing
- Runny Nose
- Itchy, Watery Eyes
- Itchy Throat

3 in 1
Fast Acting
Long Lasting
Less Drowsy

60 Tablets

Indoor & Outdoor Allergies
12-hour Extended-Release Tablets
Chlorpheniramine Maleate 12 mg/Antihistamine

PACKAGE LABEL

New Look. Same Trusted Ingredient. MADE IN USA
NDC 10702-017-01

Chlorphen-12
Allergy

- Sneezing
- Runny Nose
- Itchy, Watery Eyes
- Itchy Throat

3 in 1
Fast Acting
Long Lasting
Less Drowsy

100 Tablets

Indoor & Outdoor Allergies
12-hour Extended-Release Tablets
Chlorpheniramine Maleate 12 mg/Antihistamine

Principal Display Panel - 4 Tablets in a sachet and a carton of 50 sachets

New Look. Same Trusted Ingredient. MADE IN USA
NDC 10702-017-04

NDC 10702-017-54

Chlorphen-12
Allergy

Sneezing
Runny Nose
Itchy, Watery Eyes
Itchy Throat

3 in 1
Fast Acting
Long Lasting
Less Drowsy

4 Tablets in a sachet and a carton of 50 sachets

Indoor & Outdoor Allergies
12-hour Extended-Release Tablets
Chlorpheniramine Maleate 12 mg/Antihistamine